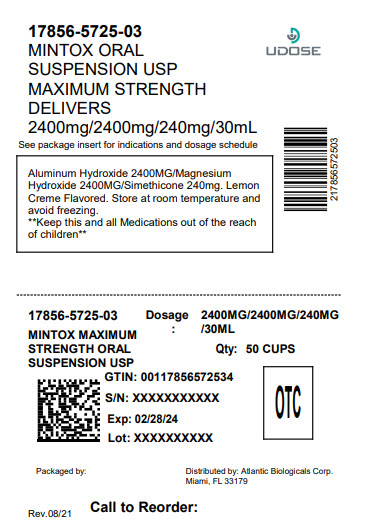 DRUG LABEL: MINTOX MAXIMUM STRENGTH
NDC: 17856-5725 | Form: SUSPENSION
Manufacturer: ATLANTIC BIOLOGICALS CORP.
Category: otc | Type: HUMAN OTC DRUG LABEL
Date: 20250731

ACTIVE INGREDIENTS: ALUMINUM HYDROXIDE 400 mg/5 mL; MAGNESIUM HYDROXIDE 400 mg/5 mL; DIMETHICONE 40 mg/5 mL
INACTIVE INGREDIENTS: BUTYLPARABEN; CARBOXYMETHYLCELLULOSE SODIUM; HYPROMELLOSES; CELLULOSE, MICROCRYSTALLINE; BENZYL ALCOHOL; PROPYLPARABEN; WATER; SACCHARIN SODIUM; SORBITOL; D&C YELLOW NO. 10; GLYCERIN

Mintox Max

Active ingredients (in each 5 mL teaspoonful)

Aluminum hydroxide 400 mg (equivalent to dried gel, USP)

Magnesium hydroxide 400 mg

Simethicone 40mg

Purposes

Antacid

Antigas

Uses

relieves

- heartburn
- sour stomach
- acid indigestion
- the symptoms referred to as gas

Warnings

Ask a doctor before use if you have

• kidney disease

• a magnesium-restricted diet

taking a prescription drug. Ask a doctor or pharmacist before use if you are

Antacids may interact with certain prescription drugs.

symptoms last more than 2 weeks Stop use and ask a doctor if

ask a health professional before use. If pregnant or breast-feeding,

Keep out of reach of children.

Directions

• shake well before use

• do not take more than 8 teaspoonfuls in 24 hours or use the maximum dosage for more than 2 weeks

• adults and children 12 years and older: take 2 to 4 teaspoonfuls two times a day, or as directed by a doctor

• children under 12 years: ask a doctor

Other information

• magnesium 165 mg, sodium 1 mg each 5 mL teaspoonful contains:

• store at room temperature

• protect from freezing

• keep tightly closed

• TAMPER-EVIDENT: Do not use if breakaway band on bottle cap is missing or broken.

Inactive ingredients

benzyl alcohol, butylparaben, caramel color, carboxymethylcellulose sodium, D and C yellow no.10, flavor, glycerin, hypromellose, microcrystalline cellulose, propylparaben, purified water, saccharin sodium, sorbitol solution